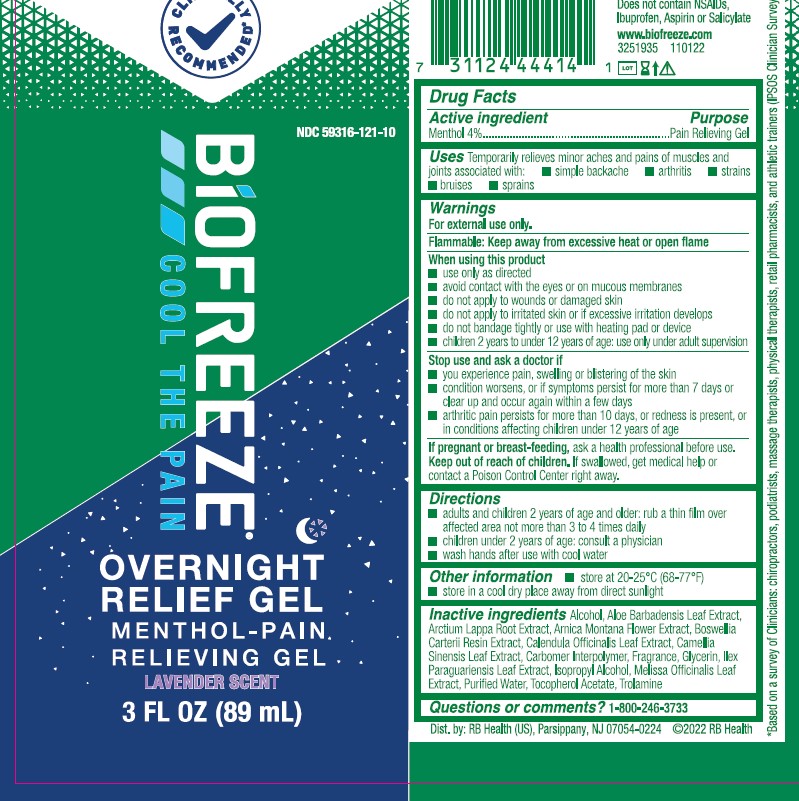 DRUG LABEL: Biofreeze Overnight Gel
NDC: 59316-121 | Form: GEL
Manufacturer: RB Health (US) LLC
Category: otc | Type: HUMAN OTC DRUG LABEL
Date: 20241227

ACTIVE INGREDIENTS: MENTHOL 40 mg/1 mL
INACTIVE INGREDIENTS: ALOE VERA LEAF; ARCTIUM LAPPA ROOT; .ALPHA.-TOCOPHEROL ACETATE; WATER; TROLAMINE; FRANKINCENSE; ARNICA MONTANA FLOWER; CALENDULA OFFICINALIS FLOWER; GREEN TEA LEAF; ALCOHOL; GLYCERIN; ILEX PARAGUARIENSIS LEAF; ISOPROPYL ALCOHOL; MELISSA OFFICINALIS LEAF; CARBOMER INTERPOLYMER TYPE A (ALLYL SUCROSE CROSSLINKED)

Biofreeze Overnight Gel

Warnings

For external use only

Flammable: Keep away from excessive heat or open flame

When using this product:

• Use only as directed • Avoid contact with the eyes or on mucous membranes • Do not apply to wounds or damaged skin • Do not apply to irritated skin or if excessive irritation develops • Do not bandage tightly or use with heating pad or device •Children 2 years to under 12 years of age:Use only under adult supervision

Stop use and ask a doctor if:

You experience pain, swelling or blistering of the skin; condition worsens, or if symptoms persist for more than 7 days, or clear up and occur again within a few days; arthritic pain persists for more than 10 days, or redness is present, or in conditions affecting children under 12 years of age

If pregnant or breastfeeding:

Ask a health professional before use

Keep out of reach of children:

If swallowed, get medical help or contact a Poison Control Center right away

Directions

¢ adults and children 2 years of age and older: rub a thin film over affected area not more than 3 to 4 times daily

¢ children under 2 years of age: consult a physician

¢ wash hands after use with cool water

Other Info

Other information

¢ store at 20-25°C (68-77°F)

¢ store in a cool dry place away from direct sunlight

Inactive Ingredients

Alcohol, Aloe Barbadensis Leaf Extract, Arctium Lappa Root Extract, Arnica Montana Flower Extract, Boswellia Carterii Resin Extract, Calendula Officinalis Leaf Extract, Camellia Sinensis Leaf Extract, Carbomer Interpolymer, Fragrance, Glycerin, Ilex Paraguariensis Leaf Extract, Isopropyl Alcohol, Melissa Officinalis Leaf Extract, Purified Water, Tocopherol Acetate, Trolamine

Questions or comments? 1-800-246-3733

Drug Facts

Dist. by: RB Health (US)
Parsippany, NJ 07054-0224

Uses

Temporarily relieves minor aches and pains of muscles and joints associated with:

¢ simple backache ¢ arthritis ¢ strains ¢ bruises ¢ sprains

Active

Active ingredient

Menthol 4% Purpose-Pain Relieving Gel

Keep out of reach of children. If swallowed, get medical help or contact a Poison Control Center right away

PURPOSE

Temporarily relieves minor aches and pains of muscles and joints associated with:

¢ simple backache ¢ arthritis ¢ strains ¢ bruises ¢ sprains

PACKAGE LABEL

NDC 59316-121-10

BiOFREEZE®

GEL

MENTHOL-PAIN
RELIEVING GEL

3 FL OZ 89 mL